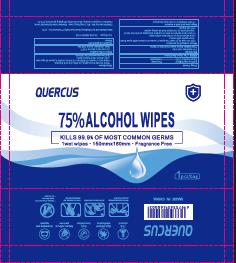 DRUG LABEL: alcohol wipes
NDC: 90017-002 | Form: CLOTH
Manufacturer: Zhejiang quercus daily necessities Co., Ltd
Category: otc | Type: HUMAN OTC DRUG LABEL
Date: 20200805

ACTIVE INGREDIENTS: ALCOHOL 0.75 g/1 g
INACTIVE INGREDIENTS: WATER

75% alcohol wipes

Active Ingredient(s)

Alcohol 75% v/v. Purpose: Antiseptic

Purpose

Antiseptic

Use

to decrease bacterial on the skin that could cause disease

Warnings

For external use only.

Do not use

- if you are allergic to any of the ingredients
- on children less than 2 years of aga unless directed by a doctor

When using this product

Avoid contact with eyes and damaged skin. In case of eye contact, flush eyes with water.

Stop use and ask a doctor if signs of irritation or rash appear

Keep out of reach of children.

Directions

Lift inner seal sticker and remove wipe. Gently wipe face and hand to clean. After use, reseal the sticker to prevent the wipes from drying out.

Other information

- Store at a shady, cool and dry place
- Avoid direct sunlight and open flames
- Wipes are insoluble in water. Please do not throw into toilet.

Inactive ingredients

water

Package Label - Principal Display Panel

1 PCS NDC 90017-002-01